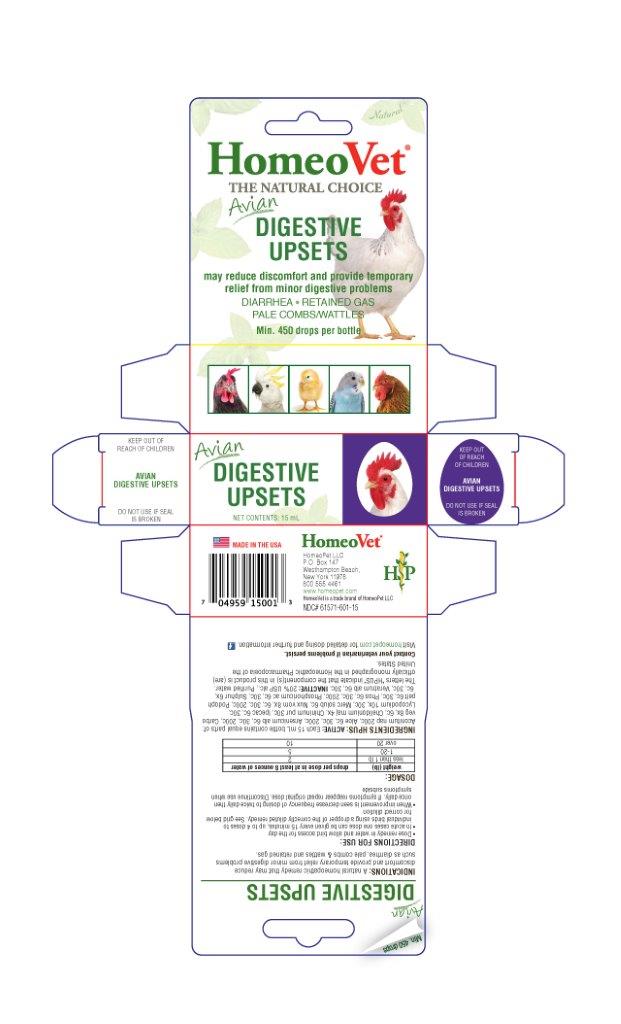 DRUG LABEL: Digestive Upsets
NDC: 61571-601 | Form: LIQUID
Manufacturer: HomeoPet, LLC
Category: homeopathic | Type: OTC ANIMAL DRUG LABEL
Date: 20201117

ACTIVE INGREDIENTS: ACONITUM NAPELLUS 200 [hp_C]/15 mL; ALOE 6 [hp_C]/15 mL; ARSENIC TRIOXIDE 6 [hp_C]/15 mL; ACTIVATED CHARCOAL 8 [hp_X]/15 mL; CHELIDONIUM MAJUS 4 [hp_X]/15 mL; QUININE  30 [hp_C]/15 mL; IPECAC 6 [hp_C]/15 mL; PHOSPHORUS 6 [hp_C]/15 mL; PHOSPHORIC ACID 6 [hp_C]/15 mL; PODOPHYLLUM PELTATUM ROOT 6 [hp_C]/15 mL; VERATRUM ALBUM ROOT 6 [hp_C]/15 mL; LYCOPODIUM CLAVATUM SPORE 10 [hp_X]/15 mL; MERCURY 6 [hp_C]/15 mL; STRYCHNOS NUX-VOMICA SEED 8 [hp_X]/15 mL; SULFUR 6 [hp_X]/15 mL
INACTIVE INGREDIENTS: ALCOHOL; WATER

Avian Digestive Upsets

Avian Digestive Upsets

May reduce discomfort and provide temporary relief from minor digestive problems

DIARRHEA - RETAINED GAS - PALE COMBS/WATTLES

Directions for Use and Dosage

- Dose remedy in water and allow bird access for the day
- In acute cases one dose can be given every 15 minutes, up to 4 doses to
  individual birds using a dropper of the correctly diluted remedy. See grid below
  for correct dilution
- When improvement is seen decrease frequency of dosing to twice daily then
  once daily. If symptoms reappear repeat original dose. Discontinue use when
  symptoms subside

weight (lb) | drops per dose in at least 8 ounces of water
less than 1lb | 2
1-20 | 5
over 20 | 10

Contact Veterinarian

Contact Veterinarian if problems persist.

Visit homeopet.com for detailed dosing and further information.

Ingredients HPUS: Active

Each 15 mL bottle contains equal parts of: Aconitum nap, 200c, Aloe 6c, 30c, 200c, Arsencium alb 6c, 30c, 200c, Carbo veg 6c, Chelidonium maj 4x, Chininum pur 30c, Ipecac 6c, 30c, Lycopodium 10x, 30c, Merc solub 6c, Nux vom 8x, 6c, 30c, 200c, Podoph pelt 6c, 30c, Phos 6c, 30c, 200c, Phosphoricum ac 6c, 30c, Sulphur 6x, 6c, 30c, Veratrum alb 6c, 30c, each at 3.22%, Carbo veg 6x at .10%.

Inactive Ingredients

USP Alcohol, Purified Water

INDICATIONS

A homeopathic remedy that may reduce discomfort and provide temporary releif from minor digestive problems such as diarrhea, plae combs & wattles and retained gas.